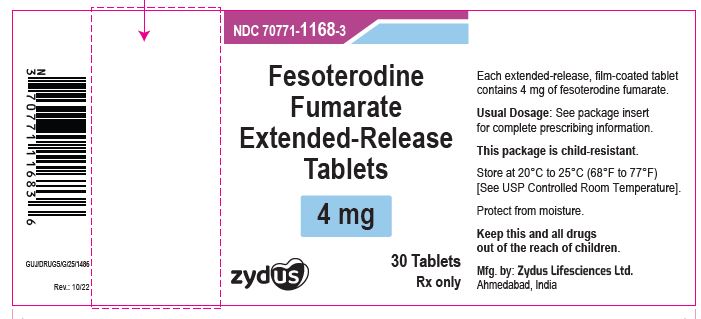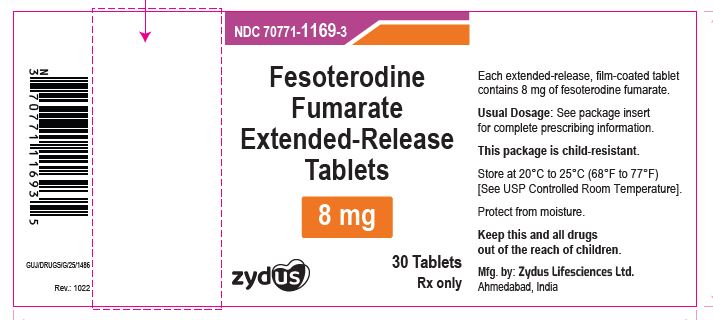 DRUG LABEL: fesoterodine fumarate
NDC: 70771-1168 | Form: TABLET, FILM COATED, EXTENDED RELEASE
Manufacturer: Zydus Lifesciences Limited
Category: prescription | Type: HUMAN PRESCRIPTION DRUG LABEL
Date: 20241130

ACTIVE INGREDIENTS: FESOTERODINE FUMARATE 4 mg/1 1
INACTIVE INGREDIENTS: STARCH, CORN; HYPROMELLOSES; LACTOSE MONOHYDRATE; LECITHIN, SOYBEAN; MAGNESIUM STEARATE; CELLULOSE, MICROCRYSTALLINE; POVIDONE; TALC; TITANIUM DIOXIDE; XANTHAN GUM; FERRIC OXIDE YELLOW; POLYVINYL ALCOHOL, UNSPECIFIED

FESOTERODINE FUMARATE EXTENDED-RELEASE TABLETS

PACKAGE LABEL.PRINCIPAL DISPLAY PANEL

NDC 70771-1168-9 in bottle of 90 tablets

Fesoterodine Fumarate Extended-release Tablets, 4 mg

Rx only

90 tablets

NDC 70771-1169-9 in bottle of 90 tablets

Fesoterodine Fumarate Extended-release Tablets, 8 mg

Rx only

90 tablets